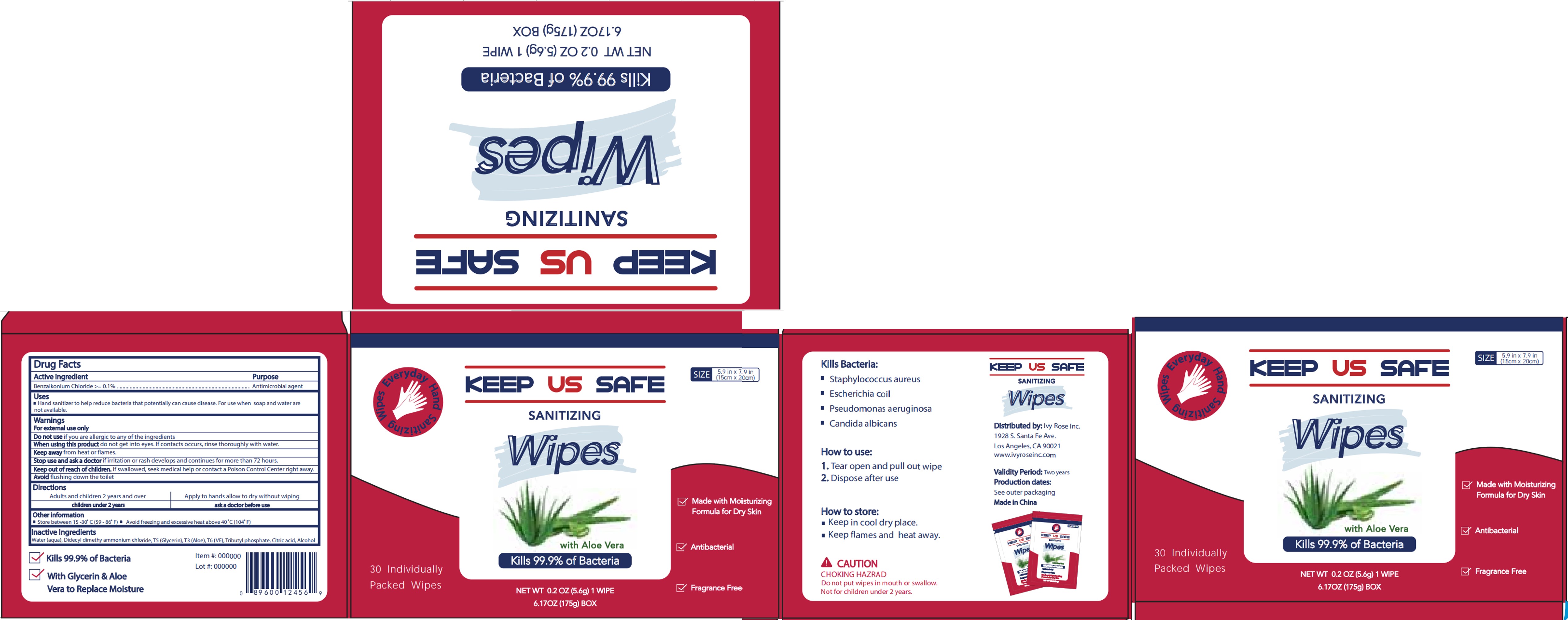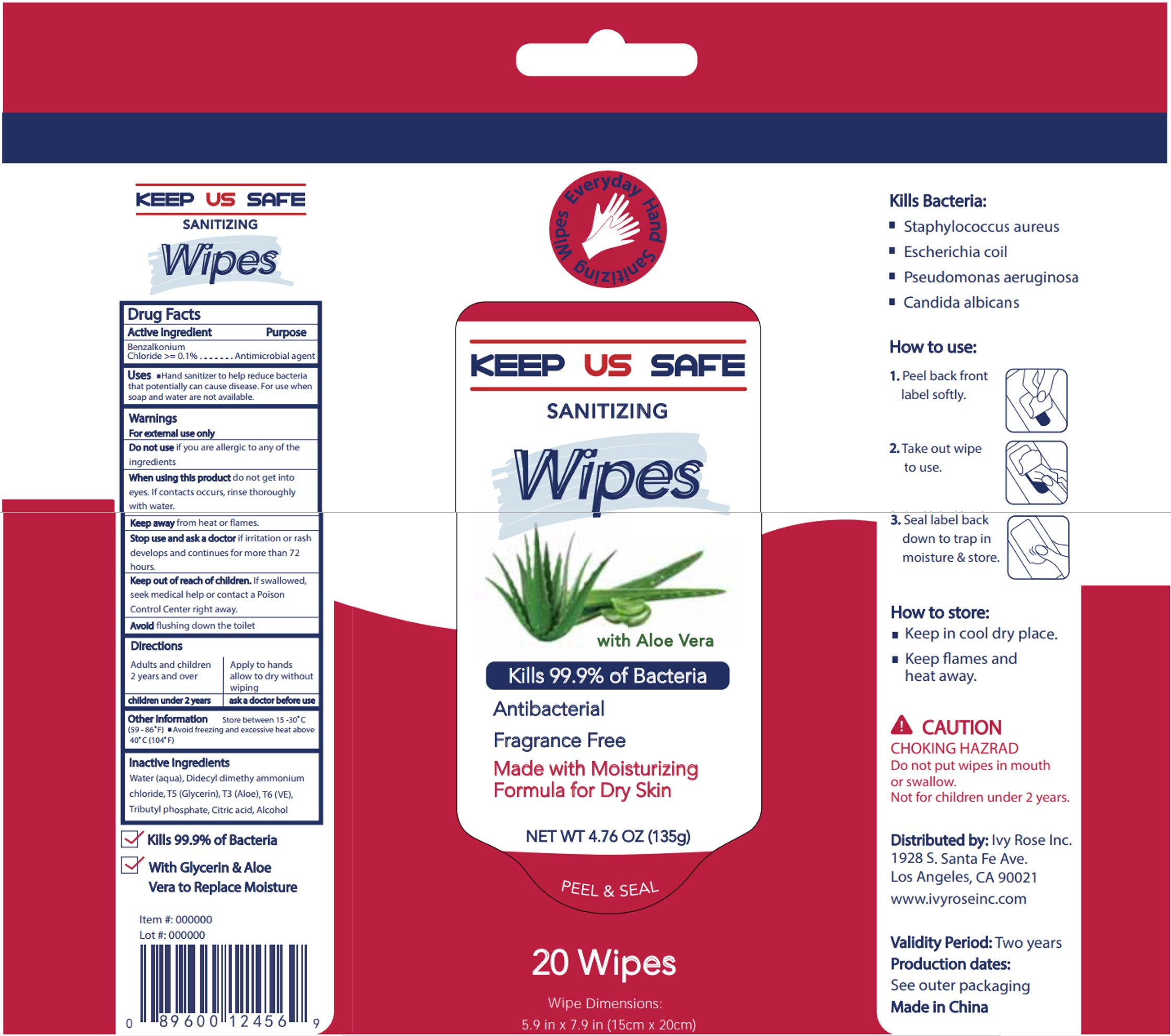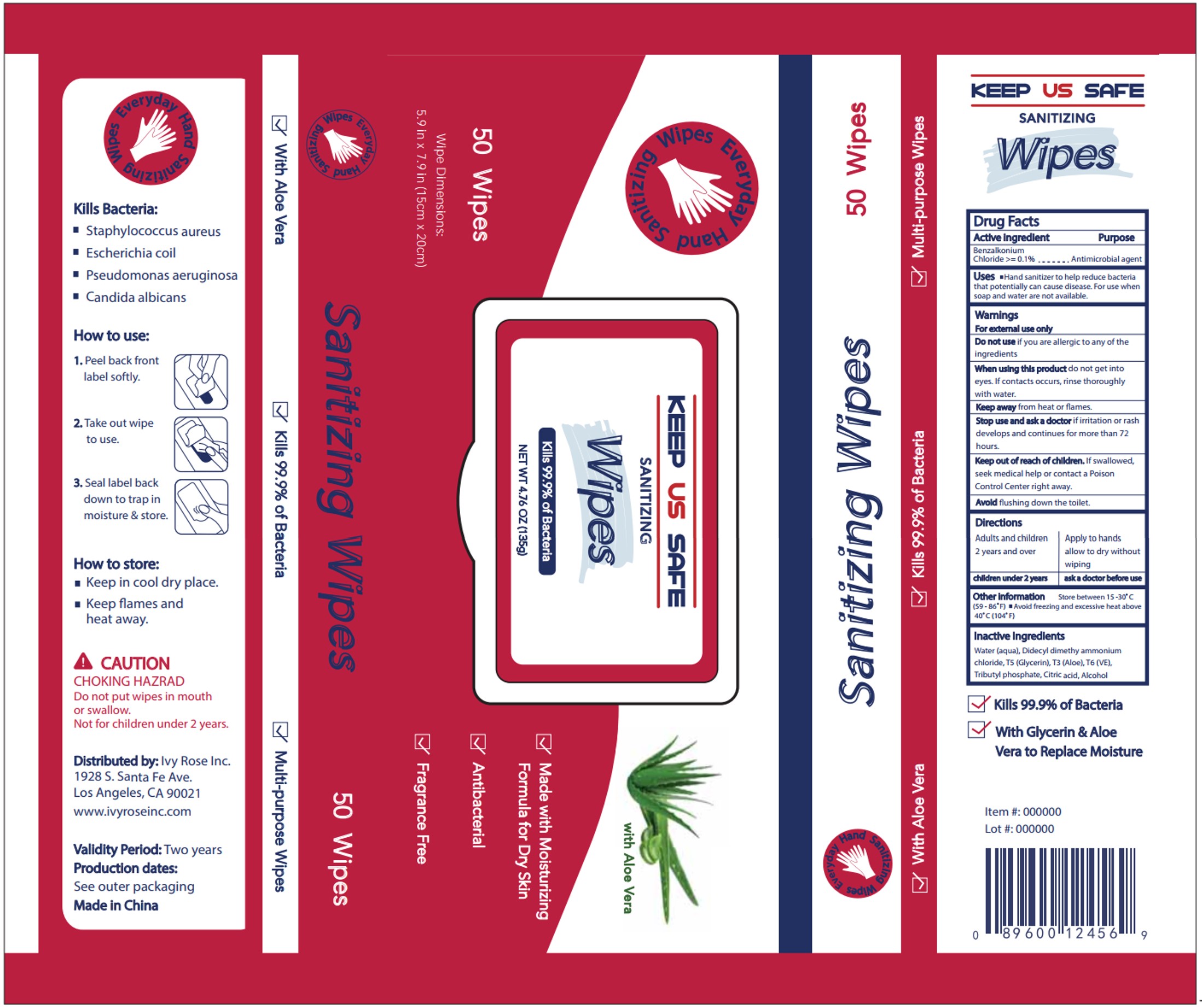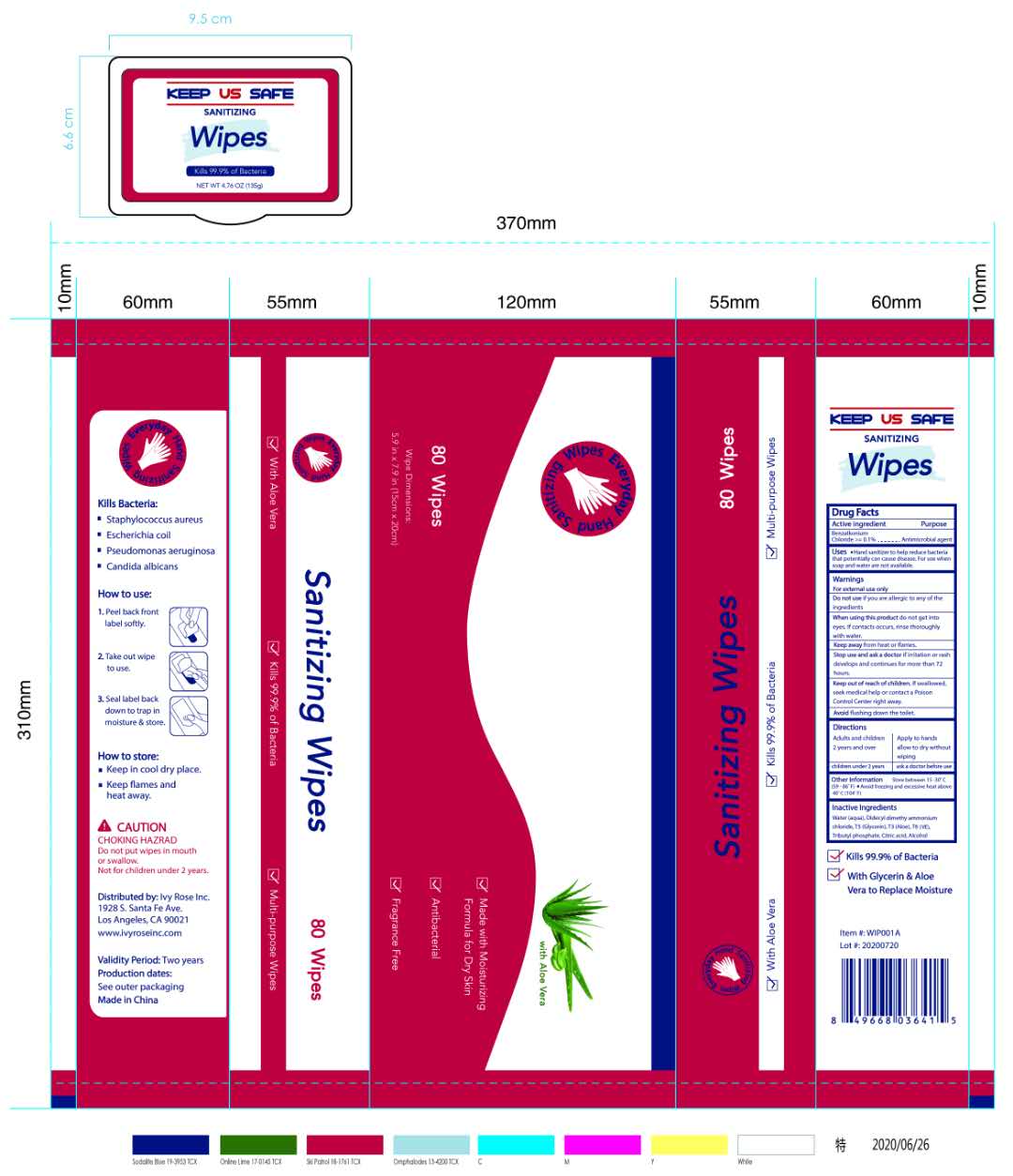 DRUG LABEL: Sanitizing Wipes
NDC: 79247-812 | Form: CLOTH
Manufacturer: Ivy Rose Inc.
Category: otc | Type: HUMAN OTC DRUG LABEL
Date: 20200812

ACTIVE INGREDIENTS: BENZALKONIUM CHLORIDE 0.1 g/100 g
INACTIVE INGREDIENTS: GLYCERIN 0.1 g/100 g; ALOE 0.0025 g/100 g; WATER 94.915 g/100 g; ALCOHOL 4.7 g/100 g; TOCOPHEROL 0.0025 g/100 g; TRI-N-BUTYL PHOSPHATE 0.01 g/100 g; DIDECYLDIMONIUM CHLORIDE 0.16 g/100 g; ANHYDROUS CITRIC ACID 0.01 g/100 g

Active Ingredient(s)

Benzalkonium chloride>=0.1%, Antimicrobial agent

Purpose

Antiseptic, Hand Sanitizer

Use

Hand Sanitizer to help reduce bacteria that potentially can cause disease. For use when soap and water are not available.

Warnings

For external use only.

Do not use

if you are allergic to any of the ingredients.

When using this product keep out of eyes, ears, and mouth. In case of contact with eyes, rinse eyes thoroughly with water.
Stop use and ask a doctor if irritation or rash occurs. These may be signs of a serious condition.
Keep out of reach of children. If swallowed, get medical help or contact a Poison Control Center right away.

Stop use and ask a doctor if irritation or rash develops and continues for more than 72 hours.

Keep out of reach of children. If swallowed, get medical help or contact a Poison Control Center right away.

Directions

- Adults and children 2 years and over.
- Apply to hands allow to dry without wiping.

Other information

- Store between 15-30C (59-86F)
- Avoid freezing and excessive heat above 40C (104F)

Inactive ingredients

Water(aqua), Didecyl dimethy ammonium chloride, T5(Glycerin), T3(Aloe), T6(VE), Tributyl phosphate, Citric acid, Alcohol.

Package Label - Principal Display Panel

30 Individually Packed Wipes in 1 BOX NDC: 79247-812-01

Package Label - Principal Display Panel

20 Wipes in 1 BOX NDC: 79247-812-02

Package Label - Principal Display Panel

50 Wipes in 1 BOX NDC: 79247-812-03

Package Label - Principal Display Panel

80 Wipes in 1 BOX NDC: 79247-812-04